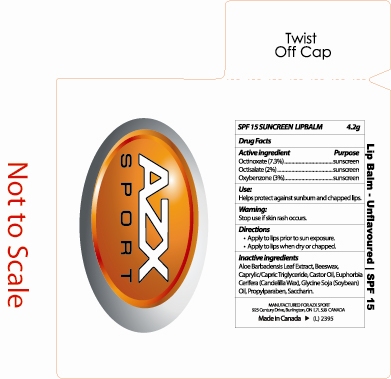 DRUG LABEL: Lip Balm
NDC: 75887-002 | Form: STICK
Manufacturer: Aztex Enterprises
Category: otc | Type: HUMAN OTC DRUG LABEL
Date: 20181221

ACTIVE INGREDIENTS: OCTINOXATE 0.3 g/4.2 g; OCTISALATE 0.08 g/4.2 g; OXYBENZONE 0.13 g/4.2 g
INACTIVE INGREDIENTS: ALOE VERA LEAF; YELLOW WAX; MEDIUM-CHAIN TRIGLYCERIDES; CASTOR OIL; CANDELILLA WAX; SOYBEAN; PROPYLPARABEN; METHYLPARABEN; SACCHARIN

Lip Balm

Uses
Helps protect against sunburn and chapped lips.

Warnings:
Stop use if skin rash occurs.

Directions
+Apply to lips prior to sun exposure
+Apply to lips when dry or chapped

Inactive Ingredients
Aloe Barbadensis Leaf Extract
Beeswax
Caprylic/Capric Triglyceride
Castor Oil
Euphorbia Cerifera(Candelilla Wax)
Glycine Soja (soybean) Oil
Propylparaben
Methylparaben
Saccharin

ACTIVE INGREDIENT

SPF 15 SUNSCREEN LIPBALM 4.2g
Drug Facts
Active Ingredient Purpose
Octinoxate (7.3%) sunscreen
Octisalate (2%) sunscreen
Oxybenzone (3%) sunscreen

PACKAGE LABEL

AZX SPORT
Lip Balm - Unlfavored l SPF 15